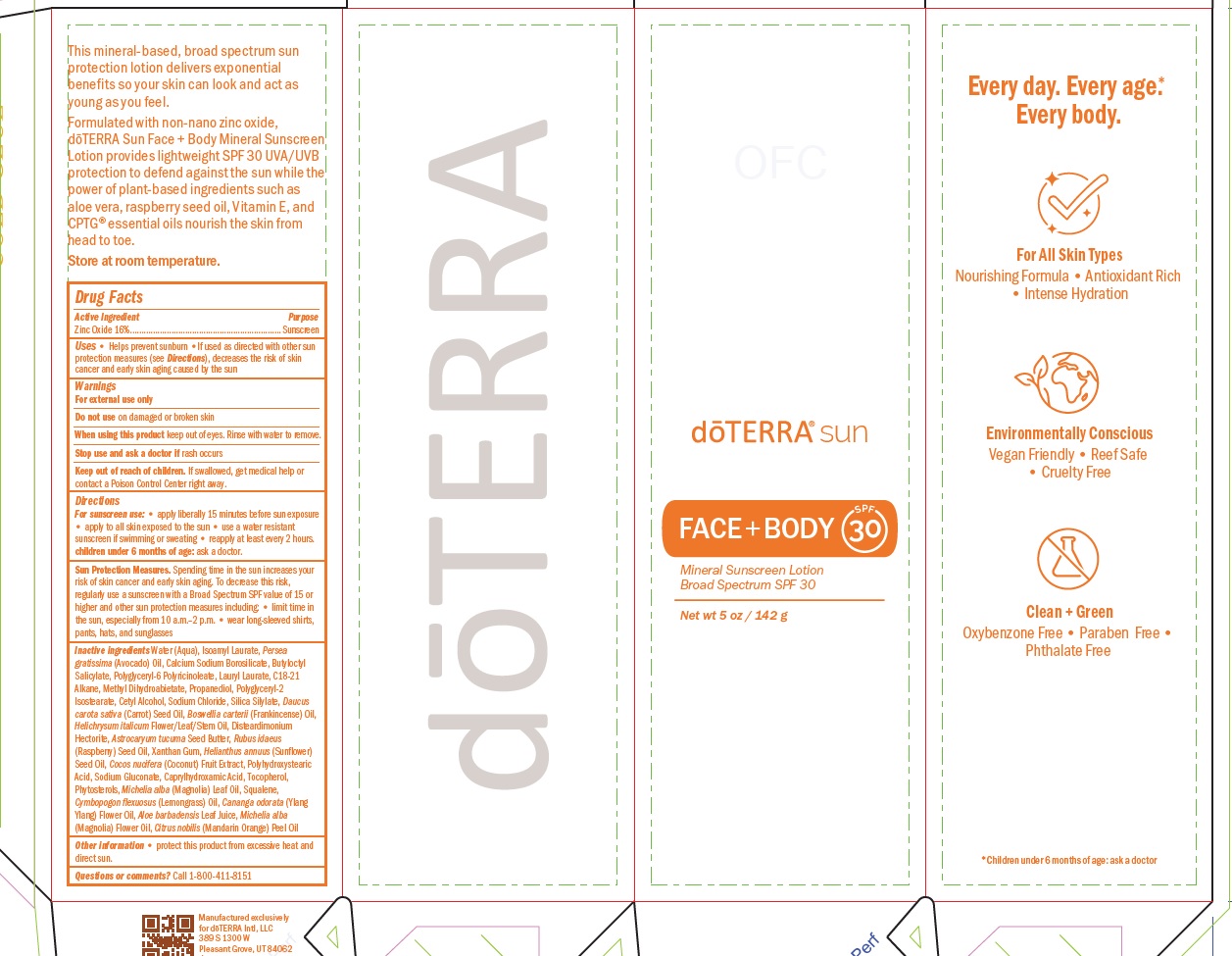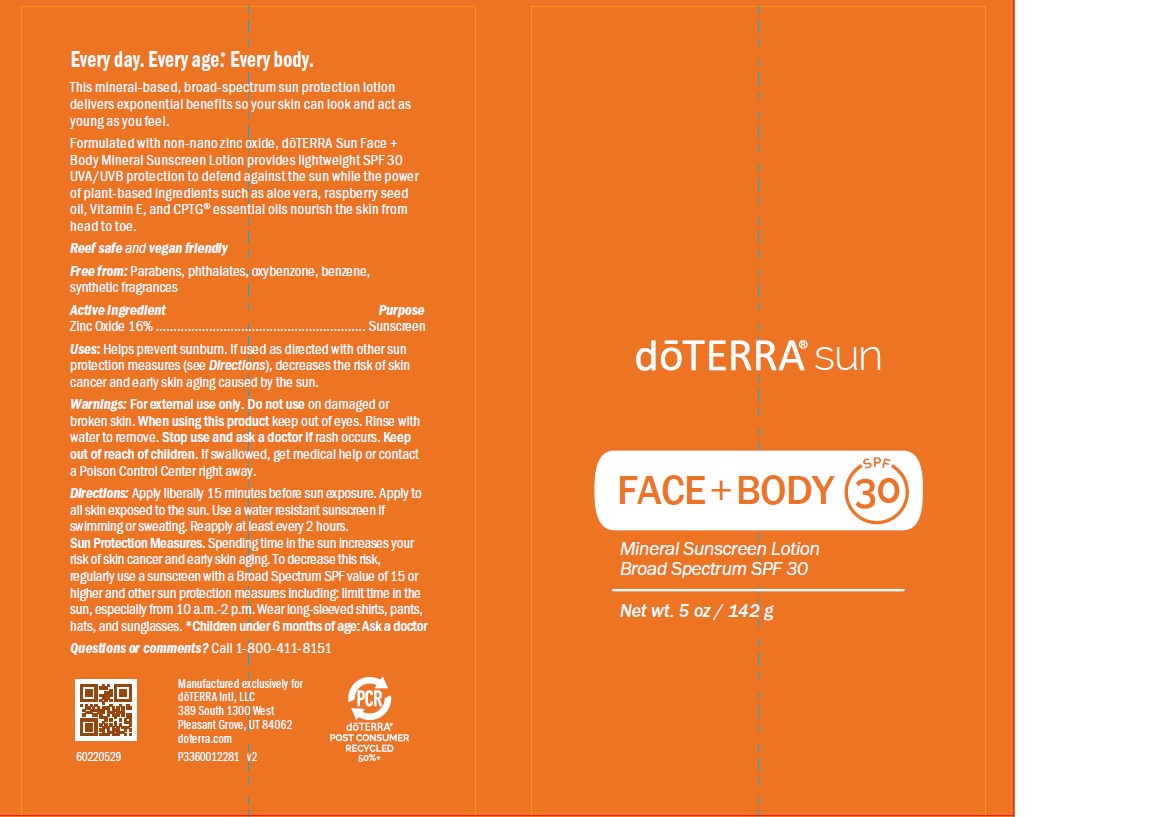 DRUG LABEL: doTERRA sun
NDC: 71630-966 | Form: LOTION
Manufacturer: doTERRA International, LLC
Category: otc | Type: HUMAN OTC DRUG LABEL
Date: 20250128

ACTIVE INGREDIENTS: ZINC OXIDE 16.3 g/100 g
INACTIVE INGREDIENTS: COCONUT OIL; CAPRYLHYDROXAMIC ACID; EAST INDIAN LEMONGRASS OIL; ISOAMYL LAURATE; AVOCADO OIL; BUTYLOCTYL SALICYLATE; HELICHRYSUM ITALICUM FLOWER OIL; ALOE VERA LEAF; CARROT SEED OIL; SODIUM BENZOATE; LAURYL LAURATE; POLYGLYCERYL-2 ISOSTEARATE; SODIUM CHLORIDE; YLANG-YLANG OIL; METHYL DIHYDROABIETATE; ASTROCARYUM MURUMURU SEED BUTTER; POLYHYDROXYSTEARIC ACID (2300 MW); SODIUM GLUCONATE; TOCOPHEROL; RASPBERRY SEED OIL; SUNFLOWER OIL; MANDARIN OIL; MICHELIA ALBA LEAF OIL; SQUALENE; POLYGLYCERYL-6 POLYRICINOLEATE; PROPANEDIOL; CETYL ALCOHOL; XANTHAN GUM; BUTYLOCTANOL; DISTEARDIMONIUM HECTORITE; FRANKINCENSE OIL; POTASSIUM SORBATE

doTERRA Sun Face and Body Mineral Sunscreen Lotion
Broad Spectrum SPF 30

ACTIVE INGREDIENT

Zinc Oxide 16%

ASK DOCTOR

Children under 6 months of age: Ask a doctor

Stop use and ask a doctor if rash occurs. Keep
out of reach of children. If swallowed, get medical help or contact
a Poison Control Center right away.

Do not use on damaged or
broken skin.

Keep
out of reach of children. If swallowed, get medical help or contact
a Poison Control Center right away.

PURPOSE

sunscreen

Questions or comments? Call 1-800-411-8151

Stop use and ask a doctor if rash occurs.

When using this product keep out of eyes. Rinse with
water to remove.

Spending time in the sun increases your
risk of skin cancer and early skin aging. To decrease this risk,
regularly use a sunscreen with a Broad Spectrum SPF value of 15 or
higher and other sun protection measures including: • limit time in
the sun, especially from 10 a.m.–2 p.m. • wear long-sleeved shirts,
pants, hats, and sunglasses

Inactive ingredients Water (Aqua), Isoamyl Laurate, Persea
gratissima (Avocado) Oil, Calcium Sodium Borosilicate, Butyloctyl
Salicylate, Polyglyceryl-6 Polyricinoleate, Lauryl Laurate, C18-21
Alkane, Methyl Dihydroabietate, Propanediol, Polyglyceryl-2
Isostearate, Cetyl Alcohol, Sodium Chloride, Silica Silylate, Daucus
carota sativa (Carrot) Seed Oil, Boswellia carterii (Frankincense) Oil,
Helichrysum italicum Flower/Leaf/Stem Oil, Disteardimonium
Hectorite, Astrocaryum tucuma Seed Butter, Rubus idaeus
(Raspberry) Seed Oil, Xanthan Gum, Helianthus annuus (Sunflower)
Seed Oil, Cocos nucifera (Coconut) Fruit Extract, Polyhydroxystearic
Acid, Sodium Gluconate, Caprylhydroxamic Acid, Tocopherol,
Phytosterols, Michelia alba (Magnolia) Leaf Oil, Squalene,
Cymbopogon flexuosus (Lemongrass) Oil, Cananga odorata (Ylang
Ylang) Flower Oil, Aloe barbadensis Leaf Juice, Michelia alba
(Magnolia) Flower Oil, Citrus nobilis (Mandarin Orange) Peel Oil

Other information • protect this product from excessive heat and
direct sun.

Directions
For sunscreen use: • apply liberally 15 minutes before sun exposure
• apply to all skin exposed to the sun • use a water resistant
sunscreen if swimming or sweating • reapply at least every 2 hours.
children under 6 months of age: ask a doctor.

INDICATIONS AND USAGE

Uses • Helps prevent sunburn •If used as directed with other sun
protection measures (see Directions), decreases the risk of skin
cancer and early skin aging caused by the sun

Warnings
For external use only
Do not use on damaged or broken skin
When using this product keep out of eyes. Rinse with water to remove.
Stop use and ask a doctor if rash occurs
Keep out of reach of children. If swallowed, get medical help or
contact a Poison Control Center right away.

Active Ingredient Purpose
Zinc Oxide 16%.................................................................. Sunscreen